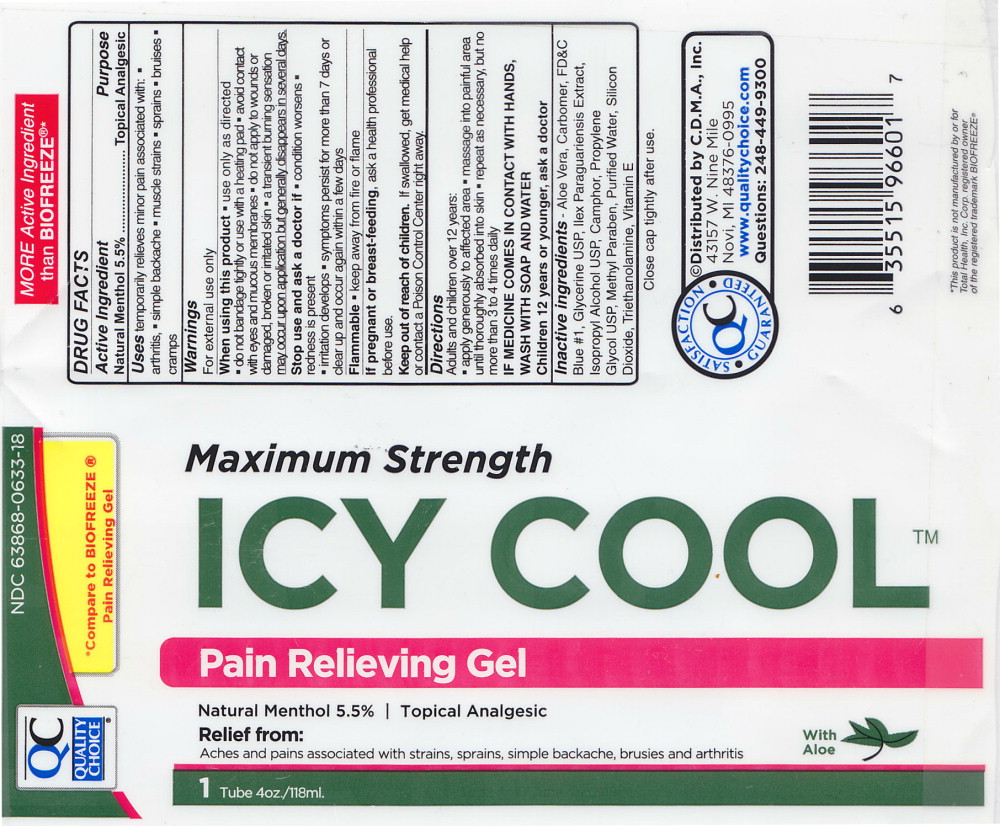 DRUG LABEL: Icy Cool 
NDC: 63868-633 | Form: GEL
Manufacturer: C.D.M.A. Inc.
Category: otc | Type: HUMAN OTC DRUG LABEL
Date: 20140814

ACTIVE INGREDIENTS: Menthol 55 mg/1 mL
INACTIVE INGREDIENTS: ALOE VERA LEAF; .ALPHA.-TOCOPHEROL ACETATE; CAMPHOR (SYNTHETIC); CARBOMER HOMOPOLYMER TYPE C (ALLYL PENTAERYTHRITOL CROSSLINKED); FD&C BLUE NO. 1; GLYCERIN; ILEX PARAGUARIENSIS LEAF; ISOPROPYL ALCOHOL; METHYLPARABEN; PROPYLENE GLYCOL; SILICON DIOXIDE; TROLAMINE; WATER

DRUG FACTS

Active Ingredient

Natural Menthol 5.5%

Purpose

Topical Analgesic

Uses

temporarily relieves minor pain associated with:

- arthritis,
- simple backache
- muscle strains
- sprains
- bruises
- cramps

Warnings

For external use only

When using this product

- use only as directed
- do not bandage tightly or use with a heating pad
- avoid contact with eyes and mucous membranes
- do not apply to wounds or damaged, broken or irritated skin
- a transient burning sensation may occur upon application but generally disappears in several days.

Stop use and ask a doctor if

- condition worsens
- redness is present
- irritation develops
- symptoms persist for more than 7 days or clear up and occur again within a few days

Flammable

- keep away from fire of flame

PREGNANCY OR BREAST FEEDING

If pregnant or breast-feeding, ask a health professional before use.

Keep out of reach of children. If swallowed, get medical help of contact a Poison Control Center right away.

Directions

Adults and children over 12 years:

- apply generously to affected area
- message into painful area until thoroughly absorbed into skin
- repeat as necessary, but no more than 3 to 4 times daily

IF MEDICINE COMES IN CONTACT WITH HANDS, WASH WITH SOAP AND WATER

Children 12 years or younger, ask a doctor

Inactive ingredients –

AloeVera, Carbomer, FD&C Blue #1, Glycerine USP, Ilex Paraguariensis Extract, Isopropyl Alcohol USP, Camphor, Propylene Glycol USP, Methyl Paraben, Purified Water, Silicon Dioxide, Triethanolamine, Vitamin E

Principal Display Panel - 4 oz. Tube Label

QC Quality Choice

NDC 63868-0633-18

*Compare to BIOFREEZE®
Pain Relieving Gel

Maximum Strength

Icy Cool TM

Pain Relieving Gel

Natural Menthol 5.5% | Topical Analgesic

Relief From:
Aches and pains associated with strains, sprains, backaches, bruises and arthritis

With Aloe

1 Tube 4oz./118ml.